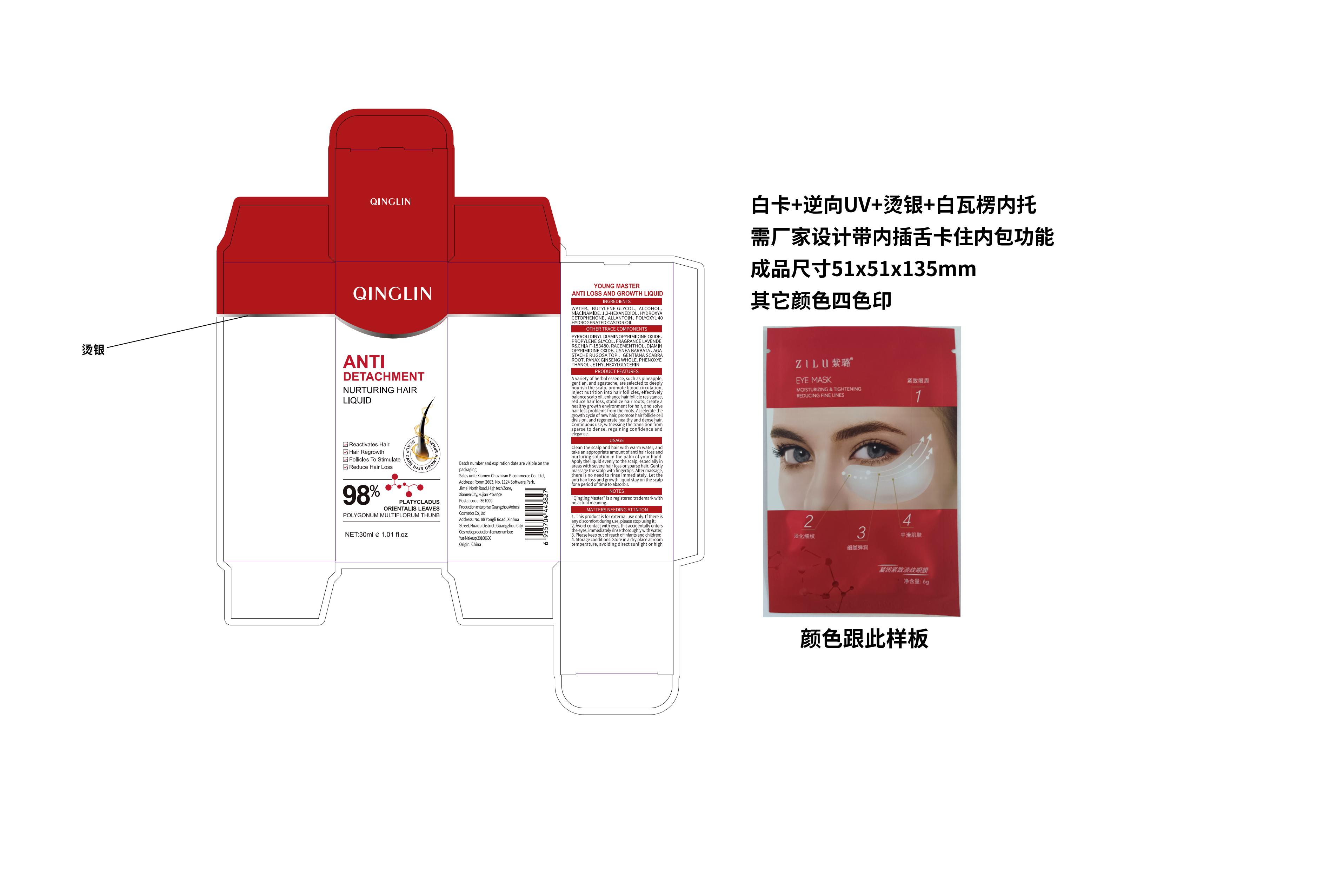 DRUG LABEL: QINGLIN ANTI DETACHMENT NURTURING HAIR
NDC: 84527-123 | Form: LIQUID
Manufacturer: Xiamen Chuzhiran E-Commerce Co., Ltd.
Category: otc | Type: HUMAN OTC DRUG LABEL
Date: 20240713

ACTIVE INGREDIENTS: PYRROLIDINYL DIAMINOPYRIMIDINE OXIDE 33 g/100 mL; PANAX GINSENG WHOLE 33 g/100 mL; DIAMINOPYRIMIDINE OXIDE 30 g/100 mL; NIACINAMIDE 33 g/100 mL
INACTIVE INGREDIENTS: BUTYLENE GLYCOL; HYDROXYACETOPHENONE; PROPYLENE GLYCOL; POLYOXYL 40 HYDROGENATED CASTOR OIL; GENTIANA SCABRA ROOT; WATER; ALCOHOL; 1,2-HEXANEDIOL; USNEA BARBATA; AGASTACHE RUGOSA TOP; ETHYLHEXYLGLYCERIN; ALLANTOIN; RACEMENTHOL; PHENOXYETHANOL; FRAGRANCE LAVENDER & CHIA F-153480

ACTIVE INGREDIENT

NIACINAMIDE,PANAX GINSENG WHOLE,PYRROLIDINYL DIAMINOPYRIMIDINE OXIDE,DIAMINOPYRIMIDINE OXIDE

INACTIVE INGREDIENT

AQUA,PROPYLENE GLYCOL,ALCOHOL,1,2-HEXANEDIOL,HYDROXYACETOPHENONE,ALLANTOIN,PEG-40 HYDROGENATED CASTOR OIL,BUTYLENE GLYCOL,MENTHOL,PHENOXYETHANOL,ETHYLHEXYLGLYCERIN

WARNINGS

Warnings section:Keep out of reach of children and pets

Keep out of reach of children, if you feel uncomfortable, please seek medical attention promptly

PURPOSE

Anti-hair loss nourishing hair

DOSAGE AND ADMINISTRATION

30ml

Wash your hair and scalp with warm water and apply the liquid to your scalp with an appropriate amount of conditioning solution in the palm of your hand, especially if you have severe hair loss or thinning hair

INDICATIONS AND USAGE

Wash your hair and scalp with warm water and apply the liquid to your scalp with an appropriate amount of conditioning solution in the palm of your hand, especially if you have severe hair loss or thinning hair